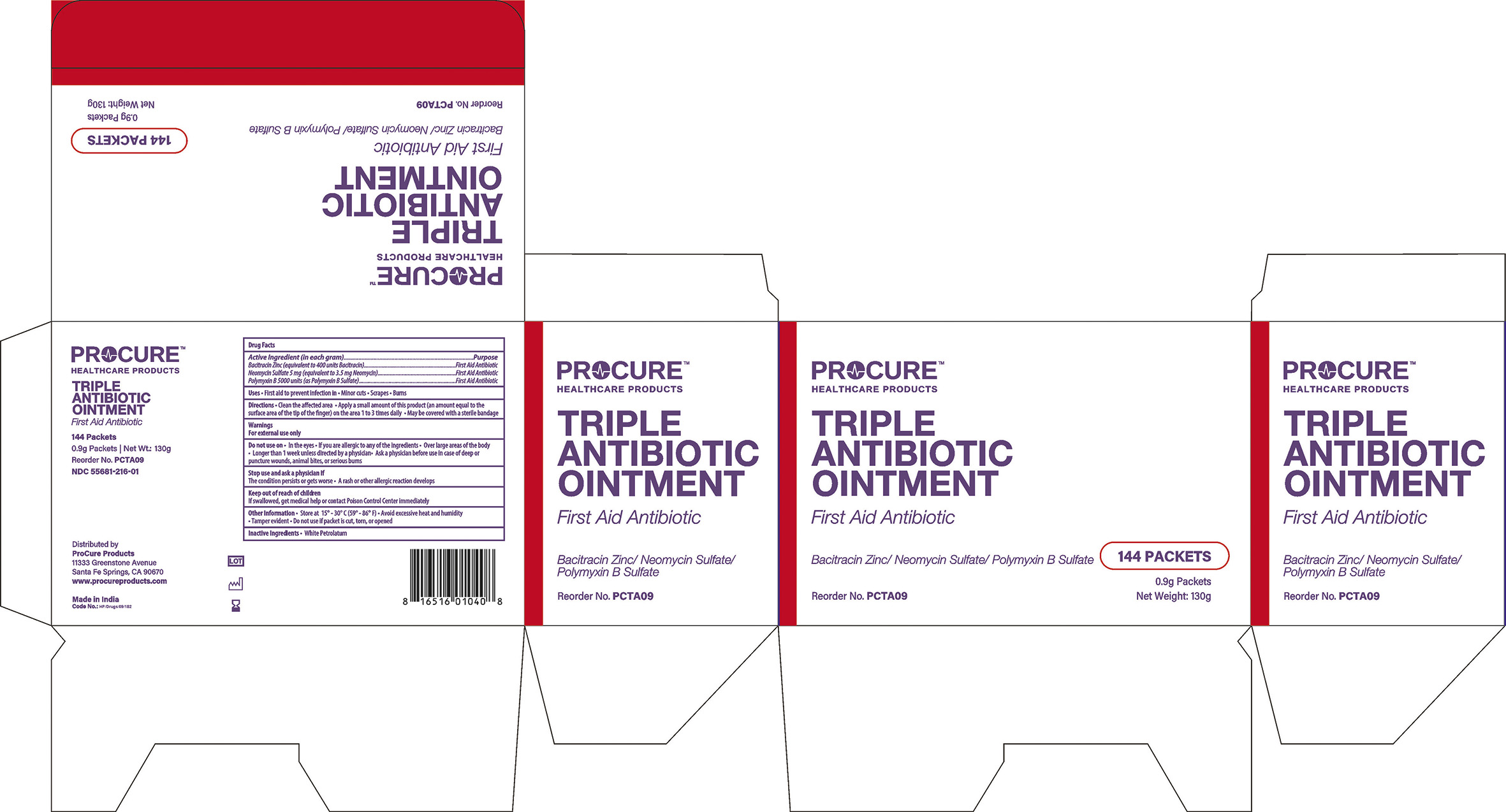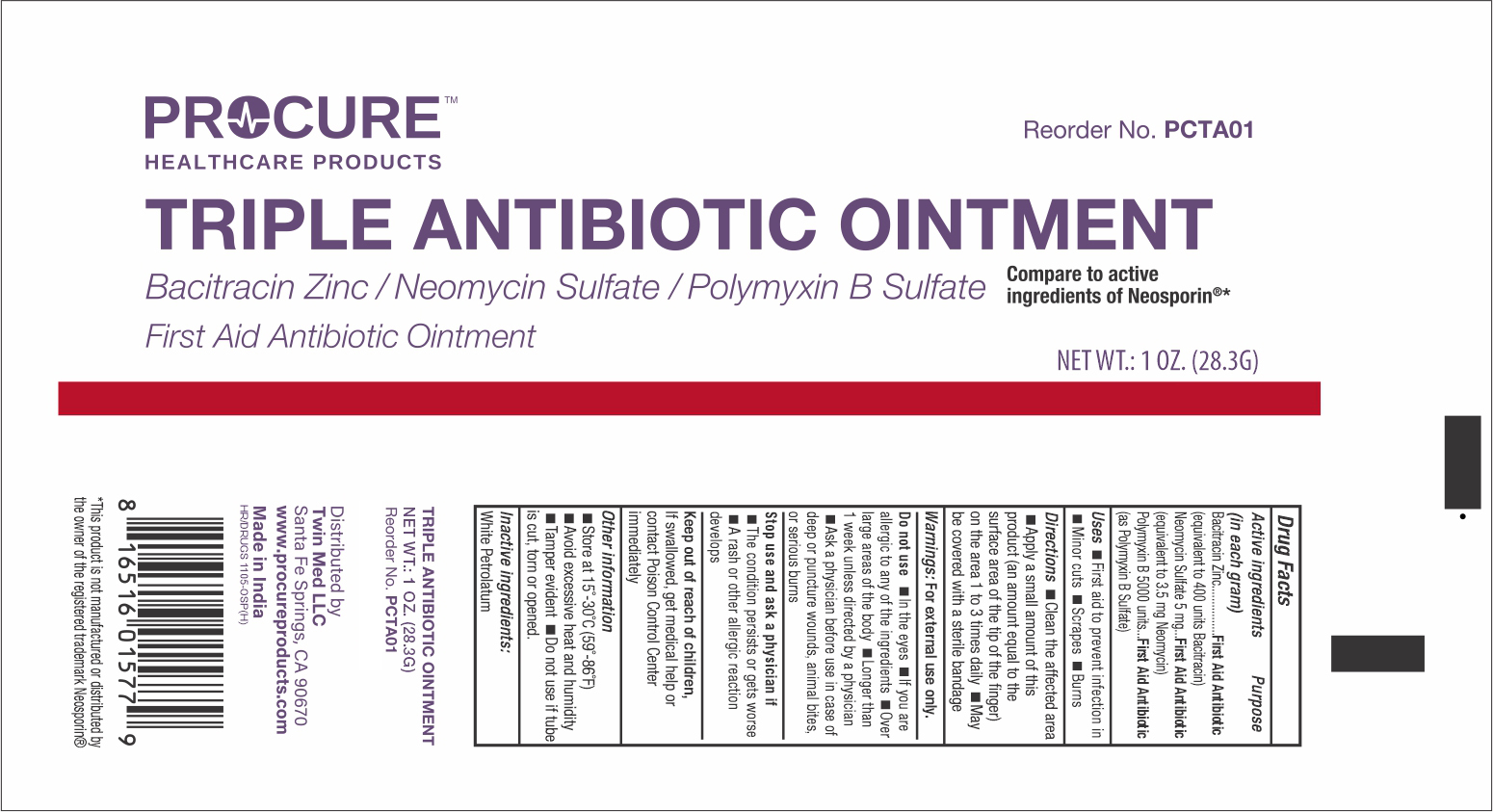 DRUG LABEL: ProcureTriple Antibiotic

NDC: 55681-216 | Form: OINTMENT
Manufacturer: TWIN MED, LLC
Category: otc | Type: HUMAN OTC DRUG LABEL
Date: 20250620

ACTIVE INGREDIENTS: BACITRACIN ZINC 400 U/1 g; NEOMYCIN SULFATE 3.5 mg/1 g; POLYMYXIN B SULFATE 5000 U/1 g
INACTIVE INGREDIENTS: PETROLATUM

Drug Facts

Active Ingredients(in each gram)

Bacitracin Zinc............400 units
Neomycin Sulfate 5mg (equivalent to 3.5 mg Neomycin)
Polymyxin B Sulfate ....5000 units

Purpose

First Aid Antibiotic

Uses

First aid to prevent infection in

- Minor cuts
- Scrapes
- Burns

Directions

- Clean the affected area
- Apply small amount of this product(an amount equal to the surface area of the tip of the finger on the area 1 to 3 times daily
- May be covered with a sterile bandage

Warnings

For External Use Only.

Do not use

- In the eyes
- If you are allergic to any of the ingredients
- Over large areas of the body
- Longer than 1 week unless directed by a doctor
- Ask a doctor before use in case of deep or puncture wounds, animal bites or serious burns

Stop use and ask a doctor if

- The condition persists or gets worse
- A rash or allergic reaction develops

Keep out of reach of children

- If swallowed, get medical help or contact a Poison Control Centre right away

Other information

- Store at controlled room temperature 15o- 30oC(59o--86oF)
- Avoid excessive heat and humidity
- Tamper Evident
- Do not use if packet is torn, cut or opened.

Inactive Ingredients

White Soft Paraffin